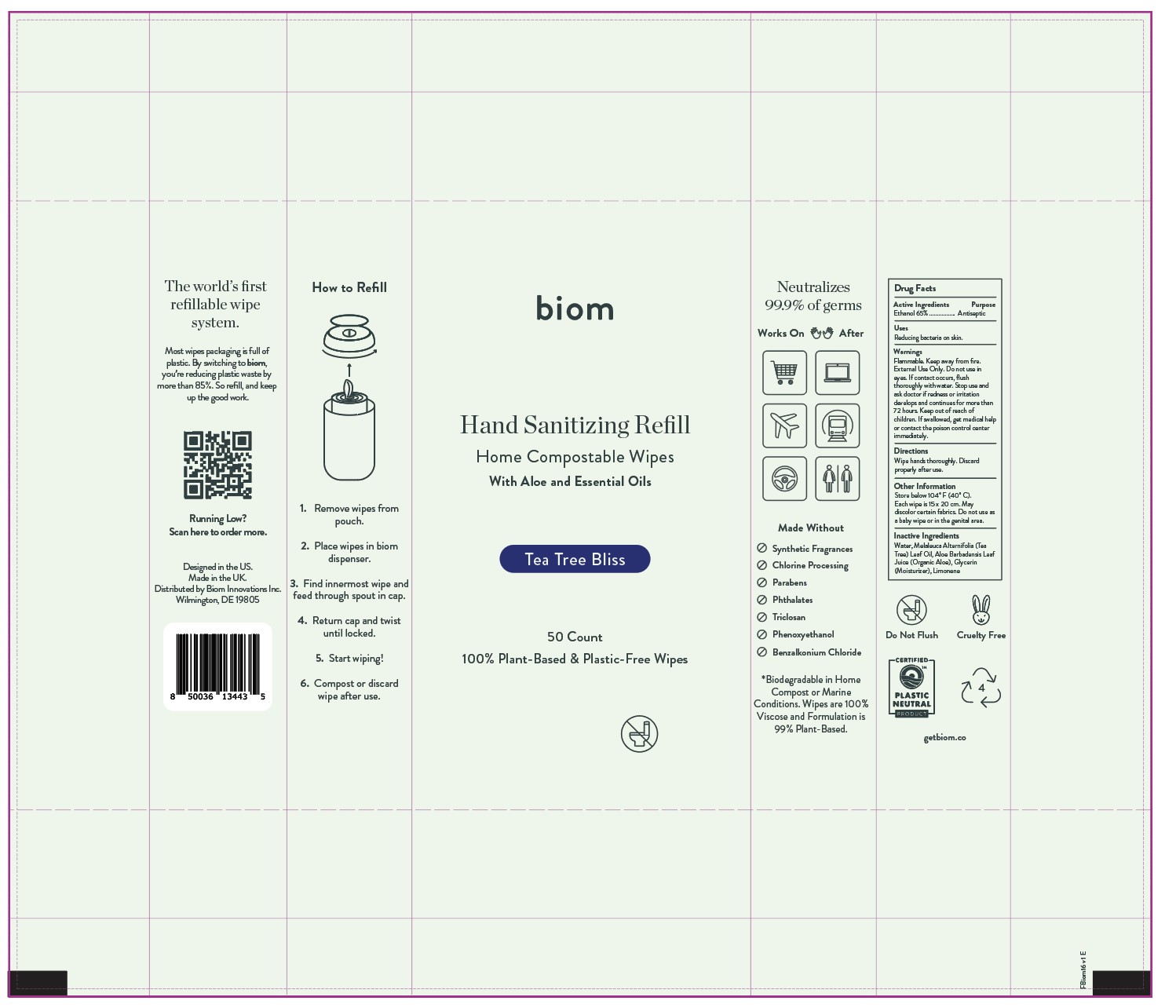 DRUG LABEL: biom Sanitizing Alcohol Wipes - Tea Tree Bliss
NDC: 82311-0118 | Form: SWAB
Manufacturer: Biom Innovations Inc
Category: otc | Type: HUMAN OTC DRUG LABEL
Date: 20241224

ACTIVE INGREDIENTS: ALCOHOL 184.1 mL/263 mL
INACTIVE INGREDIENTS: TEA TREE OIL 0.1315 mL/263 mL; ALOE VERA LEAF 2.63 mL/263 mL; GLYCERIN 2.64315 mL/263 mL; WATER 73.49535 mL/263 mL

[biom16] Sanitizing Alcohol Wipes - Tea Tree Bliss (50 wipe)

This is a hand sanitizer manufactured in compliance with (the now withdrawn) Temporary Policy for Preparation of Certain Alcohol-Based Hand Sanitizer Products During the Public Health Emergency (CoViD-19); Guidance for Industry.

The hand sanitizer is manufactured using only the following United States Pharmacopoeia (USP) grade ingredients in the preparation of the product (percentage in final product formulation) consistent with World Health Organization (WHO) recommendations:

- Alcohol (ethanol) (USP or Food Chemical Codex (FCC) grade) (65%, (w/w)) in an aqueous solution denatured according to Alcohol and Tobacco Tax and Trade Bureau regulations in 27 CFR part 20.

Active Ingredient(s)

Alcohol 65% w/w. Purpose: Antiseptic

Purpose

Reducing bacteria on skin.

Directions

Wipe hands thoroughly. Discard after use.

Warnings

Flammable. Keep away from Fire and Flame. External Use Only. Do not use in eyes. If contact occurs, flush thoroughly with water. Stop use and ask doctor if redness or irritation develops and continues for more than 72 hours. Keep out of reach of children. If swallowed, get medical help or contact the poison control center immediately.

Keep out of reach of children. If swallowed, get medical help or contact the poison control center immediately.

Stop use and ask a doctor if redness or irritation develops and continues for more than 72 hours.

Other information

Store below 104° F (40° C).
Each wipe is 15 x 20 cm.
May discolor certain fabrics.
Do not use as a baby wipe, on
the face, or in the genital area.

Inactive ingredients

Water, Tea Tree Oil, Aloe Barbadensis Leaf Juice (Organic Aloe), Glycerin (Moisturizer)

Dosage and Administration

Ethanol 65%. Wipe hands thoroughly. Discard after use.

Package Label - Principal Display Panel

50 wipes; NDC: 82311-0118-1, Hand Sanitizing Tea Tree Bliss